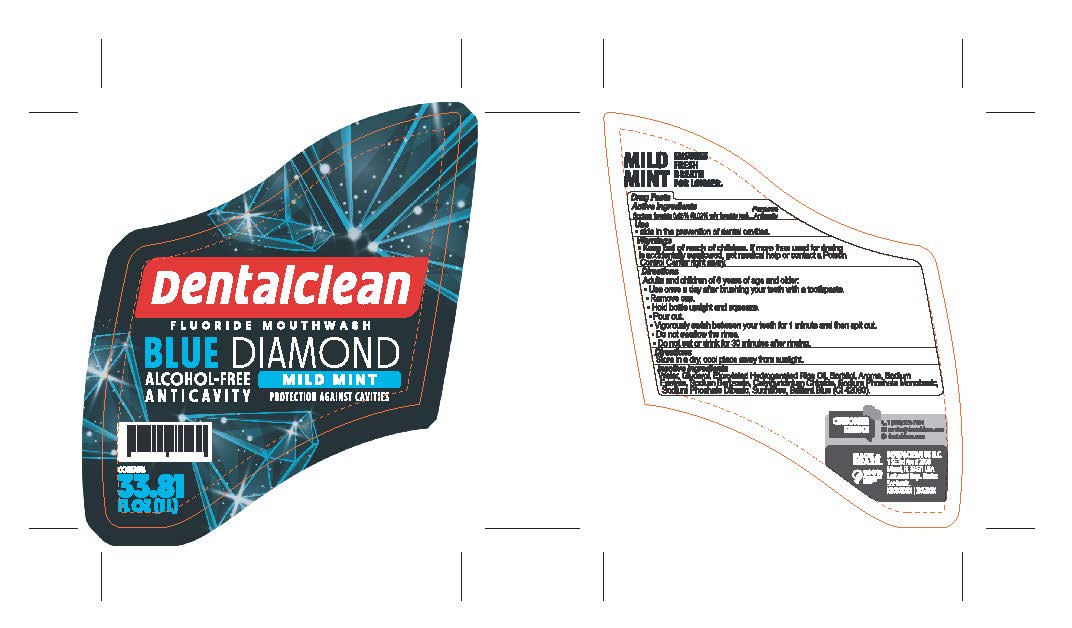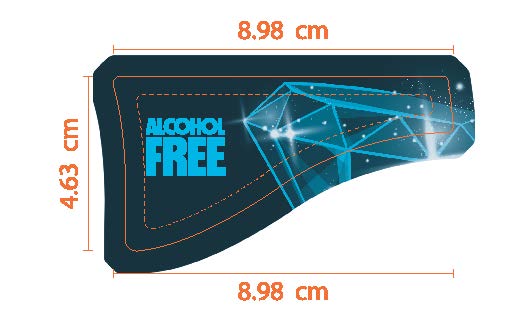 DRUG LABEL: Dentalclean Blue Diamond Alcohol Free Mouthwash
NDC: 84035-009 | Form: RINSE
Manufacturer: Rabbit Indústria e Comércio de Produtos de Higiene Pessoal Ltda
Category: otc | Type: HUMAN OTC DRUG LABEL
Date: 20240515

ACTIVE INGREDIENTS: SODIUM FLUORIDE 0.2 mg/1 mL
INACTIVE INGREDIENTS: SUCRALOSE; CETYLPYRIDINIUM CHLORIDE ANHYDROUS; TETRASODIUM EDETATE DIHYDRATE; WATER; SODIUM PHOSPHATE, MONOBASIC, MONOHYDRATE; SORBITOL; FD&C BLUE NO. 1; SODIUM BENZOATE; SODIUM PHOSPHATE DIBASIC DIHYDRATE; GLYCEROL FORMAL; POLYOXYL 60 HYDROGENATED CASTOR OIL

Dentalclean Blue Diamond Alcohol Free Mouthwash

ACTIVE INGREDIENT

Sodium fluoride 0.05%

PURPOSE

Anticavity

INDICATIONS AND USAGE

Useaids in the prevention of dental cavities

WARNINGS

WARNINGS: If more than used for brushing is accidentally swallowed, get medical help or contact poison control center right away.

Directions

Adults and children of 6 years of age and older:

• Use once a day after brushing your teeth with a toothpaste.
•Remove cap
• Hold bottle upright and squeeze
•Pour out
•Vigorously swish between your teeth for 1 minute and then spit out
• Do not swallow the rinse.
• Do not eat or drink for 30 minutes after rinsing.

OTHER SAFETY INFORMATION

Store in a dry, cool place away from sunlight.

Inactive Ingredients

Water, Glycerol, Ethoxylated Hydrogenated Rice Oil, Sorbitol, Aroma, Sodium Edetate, Sodium Benzoate, Cetylpyridinium Chloride, Sodium Phosphate Monobasic, Sodium Phosphate Dibasic, Sucralose, Brilliant Blue (CI 42090)

Keep out of reach of children under 6 years of age